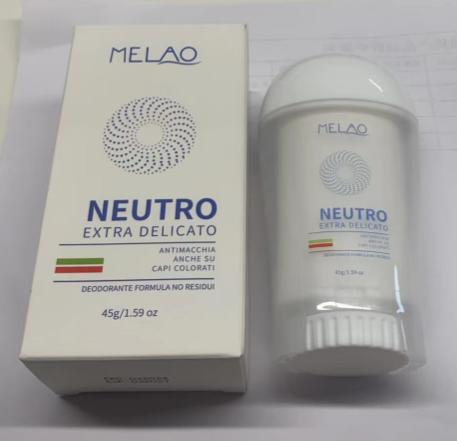 DRUG LABEL: MELAO NEUTRO EXTRA DELICATO
NDC: 83566-569 | Form: STICK
Manufacturer: Guangzhou Yilong Cosmetics Co., Ltd
Category: otc | Type: HUMAN OTC DRUG LABEL
Date: 20240807

ACTIVE INGREDIENTS: PEG-8 BEESWAX 6 g/100 g; COCOS NUCIFERA WHOLE 3.7 g/100 g
INACTIVE INGREDIENTS: MAGNESIUM HYDROXIDE 9 g/100 g; PEG-4 SORBITAN STEARATE 2.4 g/100 g; GLYCERYL STEARATE SE 3.6 g/100 g; .BETA.-BISABOLOL 1 g/100 g; ISOPROPYLPARABEN 0.07 g/100 g; .ALPHA.-TOCOPHEROL ACETATE 2 g/100 g; ETHYLHEXYL PALMITATE 5 g/100 g; DIMETHICONE CROSSPOLYMER (450000 MPA.S AT 12% IN CYCLOPENTASILOXANE) 55 g/100 g; PARAFFIN 4 g/100 g; AROMADENDRIN 2.3 g/100 g; BLUE MORWONG, COOKED 0.93 g/100 g

Active ingredients

Beeswax6%

Cocos Nucifera (Coconut)Oil3.7%

Inactive ingredients

Cyclopentasiloxane55%

Magnesium Hydroxide9%

Ethylhexyl Palmitate5%

Ozokerite 5%

paraffin4%

Glyceryl Stearate3.6%

Sorbitan Stearate2.4%

Aroma2.3%

Tocopherol2%

Bisabolol1%

BHT0.93%

Propylparaben0.07%

Purpose

Deodorization

Uses

STEP1: Clean and thoroughly dry your skin.

STEP2: Twist the bottom of the product.

STEP3: Gently apply to the underarms or other desired areas.

Warnings

For external use only.

Stop use and ask a doctor if

rash occurs.

Do not use

on damaged or broken skin

When using this product

keep out of eyes. Rinse withwater to remove.

Keep out of reach of children.

If swallowed, get medical help or contact a Poison Control Center right away.

DOSAGE & ADMINISTRATION

Squeeze out an appropriate amount of sunscreen and spread evenly on skin.